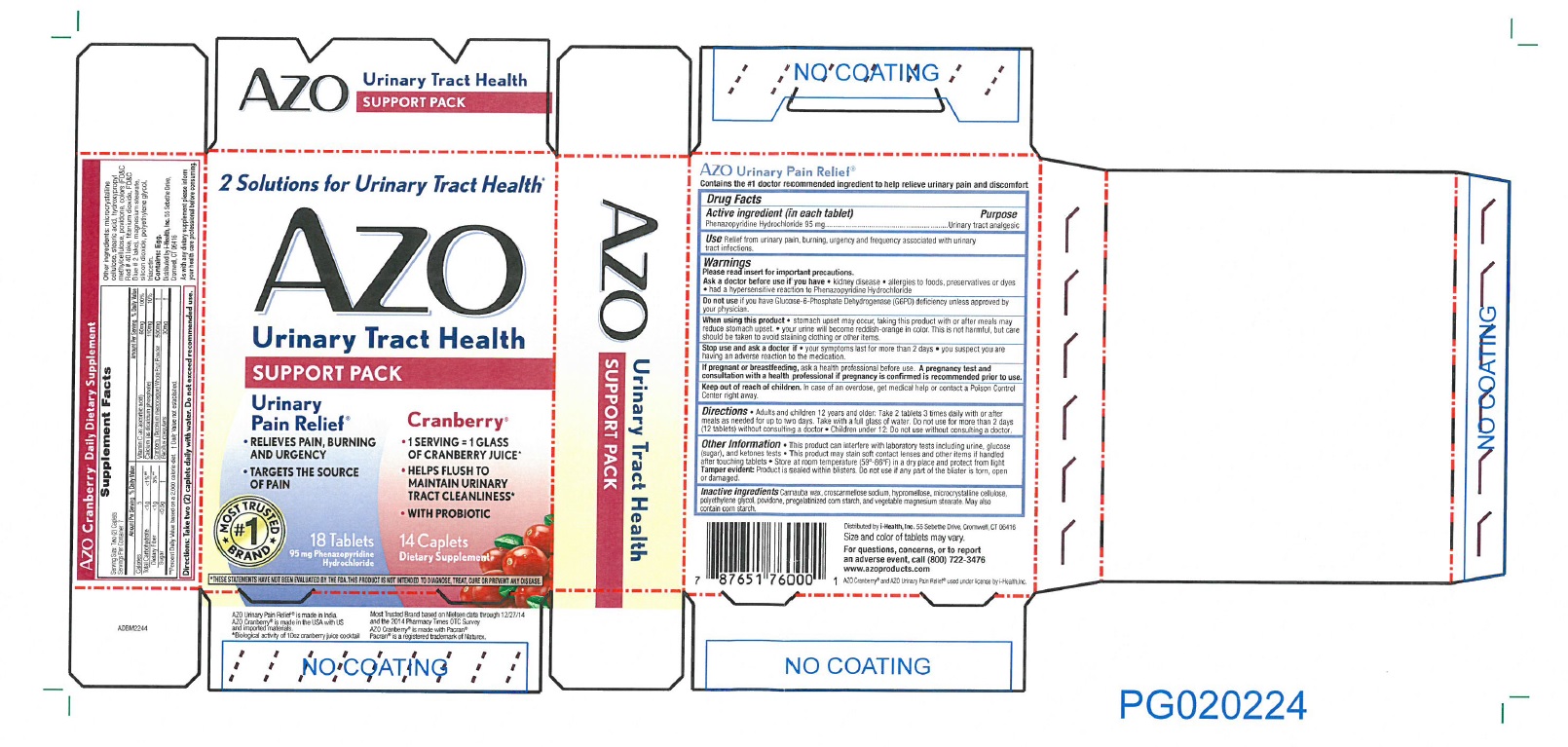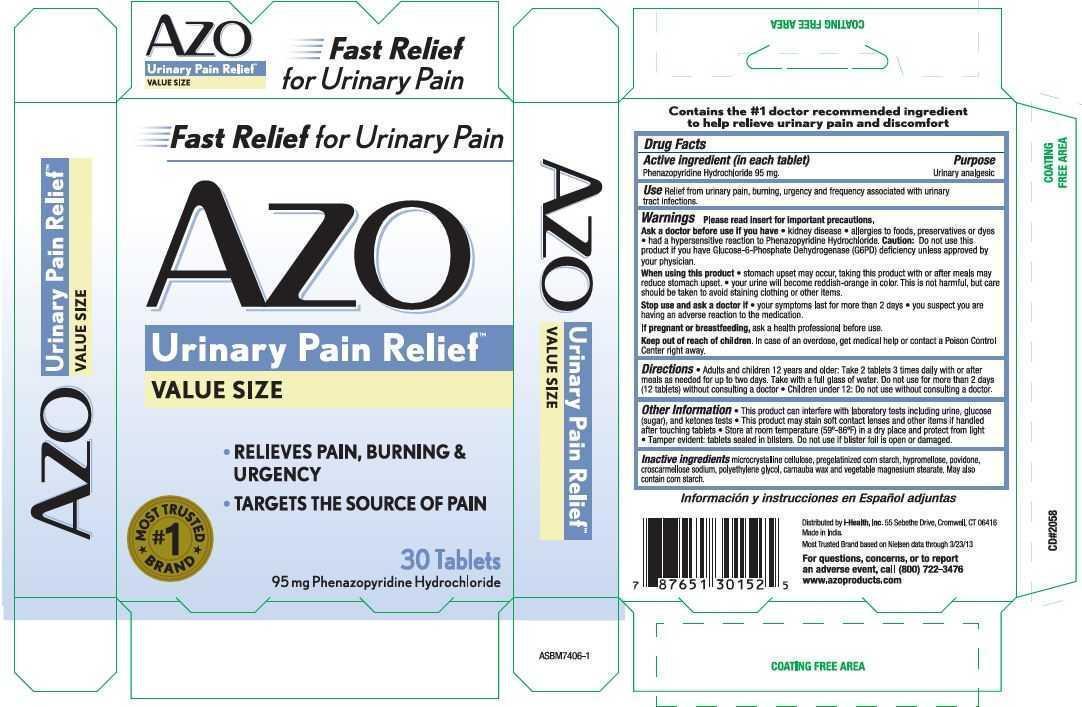 DRUG LABEL: AZO
NDC: 49973-301 | Form: TABLET
Manufacturer: i-Health, Inc.
Category: otc | Type: HUMAN OTC DRUG LABEL
Date: 20260105

ACTIVE INGREDIENTS: PHENAZOPYRIDINE HYDROCHLORIDE 95 mg/1 1
INACTIVE INGREDIENTS: CELLULOSE, MICROCRYSTALLINE; STARCH, CORN; HYPROMELLOSES; POVIDONE, UNSPECIFIED; CROSCARMELLOSE SODIUM; POLYETHYLENE GLYCOL, UNSPECIFIED; CARNAUBA WAX; MAGNESIUM STEARATE

AZO Urinary Pain Relief

Drug Facts

Active ingredient (in each tablet)

Phenazopyridine Hydrochloride 95 mg

Purpose

Urinary analgesic

INDICATIONS AND USAGE

UseRelief from urinary pain, burning, urgency and frequency associated with urinary tract infections.

Warnings Please read insert for important precautions.

Ask a doctor before use if you have

- kidney disease
- allergies to foods, preservatives or dyes
- had a hypersensitive reaction to Phenazopyridine Hydrochloride.

DO NOT USE

Caution:Do not use this product if you have Glucose-6-Phosphate Dehydrogenase (G6PD) deficiency unless approved by your physician.

When using this product

- stomach upset may occur, taking this product with or after meals may reduce stomach upset.
- your urine will become reddish-orange in color. This is not harmful, but care should be taken to avoid staining clothing or other items.

Stop use and ask doctor

- your symptoms last for more than 2 days
- you suspect you are having an adverse reaction to the medication.

Keep out of reach of children. In case of an overdose, get medical help or contact a Poison Control Center right away.

Directions

- Adults and children 12 years or older: Take 2 tablets 3 times daily with or after meals as needed for up to two days. Take with a full glass of water. Do not use for more than 2 days (12 tablets) without consulting a doctor.
- Children under 12: Do not use without consulting a doctor.

GENERAL PRECAUTIONS

Other Inf ormation

- This product can interfere with laboratory tests including urine, glucose (sugar), and ketones tests
- This product may stain soft contact lenses and other items if handled after touching tablets
- Store at room temperature (59-86 F) in a dry place and protect from light
- Tamper evident: tablets sealed in blisters. Do not use if blister foil or seal is open or damaged.

INACTIVE INGREDIENT

Inactive ingredientsmicrocrystalline cellulose, pregelatinized corn starch, hypromellose, povidine, croscarmellose sodium, polyethylene glycol, carnauba wax and vegetable magnesium stearate. May also contain corn starch.

QUESTIONS

Distributed by i-Health, Inc.

25 Bacon Road, Enfield, CT 06082

Made in India.

Most Trusted Brand based on Nielsen data through 3/23/2013.

For questions, concerns, or to report an adverse event, call (800) 722-3476

www.azoproducts.com

PACKAGE LABEL

AZO

Urinary Pain Relief

- Relieves pain, burning & urgency
- Targets the source of pain

#1 Most Trusted Brand

Tablets

95 mg Phenazopyridine Hydrochloride